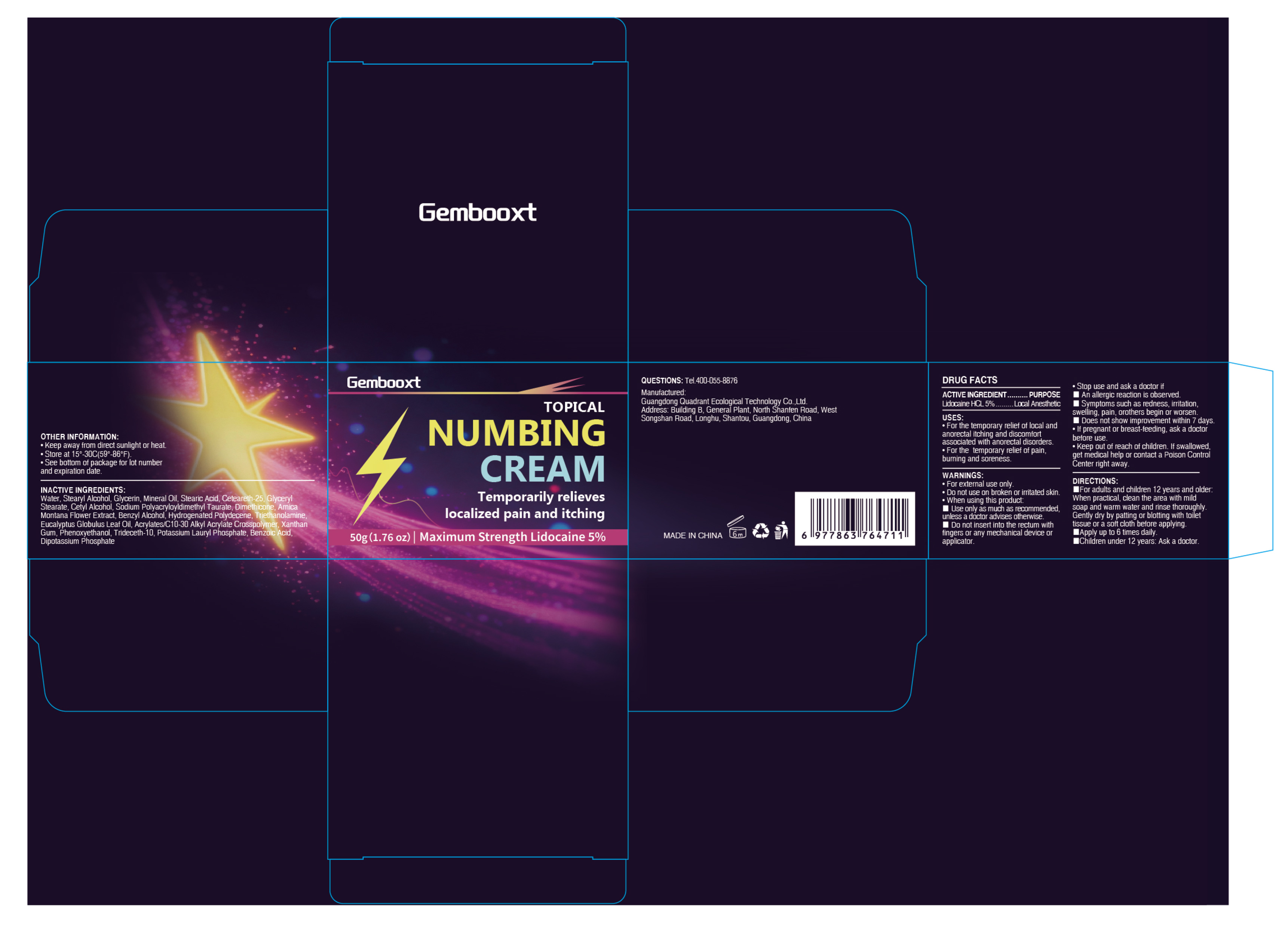 DRUG LABEL: Gembooxt Topical Numbing Cream
NDC: 76986-023 | Form: CREAM
Manufacturer: Guangdong Quadrant Ecological Technology Co., Ltd.
Category: otc | Type: HUMAN OTC DRUG LABEL
Date: 20260130

ACTIVE INGREDIENTS: LIDOCAINE HCL 0.05 g/1 g
INACTIVE INGREDIENTS: TRIDECETH-10; DIMETHICONE; PHENOXYETHANOL; SODIUM POLYACRYLOYLDIMETHYL TAURATE; POTASSIUM LAURYL PHOSPHATE; STEARIC ACID; GLYCERIN; XANTHAN GUM; STEARYL ALCOHOL; CETEARETH-25; GLYCERYL STEARATE; DIBASIC POTASSIUM PHOSPHATE; TRIETHANOLAMINE; ARNICA MONTANA FLOWER; HYDROGENATED POLYDECENE (1500 CST); BENZOIC ACID; ACRYLATES/C10-30 ALKYL ACRYLATE CROSSPOLYMER (60000 MPA.S); EUCALYPTUS GLOBULUS OIL; CETYL ALCOHOL; MINERAL OIL; WATER; BENZYL ALCOHOL

76986-023 Gembooxt Topical Numbing Cream

ACTIVE INGREDIENT

LIDOCAINE HCL 5%

PURPOSE

Local Anesthetic

INDICATIONS AND USAGE

For the temporary relief of local and anorectal itching and discomfort associated with anorectal disorders.
For the temporary relief of pain,bumning and soreness

WARNINGS

For external use only

Do not use on broken or irritated skin.

When using this product:
Use only as much as recommended,unless a doctor advises otherwise.
Do not insert into the rectum with fingers or any mechanical device or applicator.

Stop use and ask a doctor if
An allergic reaction is observed Symptoms such as redness, irritation,swelling, pain, orothers begin or worsen.
Does not show improvement within 7 days If pregnant or breast-feeding, ask a doctor before use.

Keep out of reach of children. lf swallowed get medical help or contact a Poison Gontrol Center right away

DOSAGE AND ADMINISTRATION

For adults and children 12 years and older:
When practical, clean the area with mild soap and warm water and rinse thoroughly Gently dry by patting or blotting with toilet tissue or a soft cloth before applying.
Apply up to 6 times daily.
Children under 12 years. Ask a doctor.

INACTIVE INGREDIENT

WATER
CETYL ALCOHOL
STEARYL ALCOHOL
GLYCERIN
MINERAL OIL
SODIUM POLYACRYLOYLDIMETHYL TAURATE
HYDROGENATED POLYDECENE
TRIDECETH-10
CETEARETH-25
STEARIC ACID
GLYCERYL STEARATE
DIMETHICONE
BENZYL ALCOHOL
PHENOXYETHANOL
BENZOIC ACID
ARNICA MONTANA FLOWER EXTRACT
TRIETHANOLAMINE
EUCALYPTUS GLOBULUS LEAF OIL
ACRYLATES/C10-30 ALKYL ACRYLATE CROSSPOLYMER
XANTHAN GUM
POTASSIUM LAURYL PHOSPHATE
DIPOTASSIUM PHOSPHATE